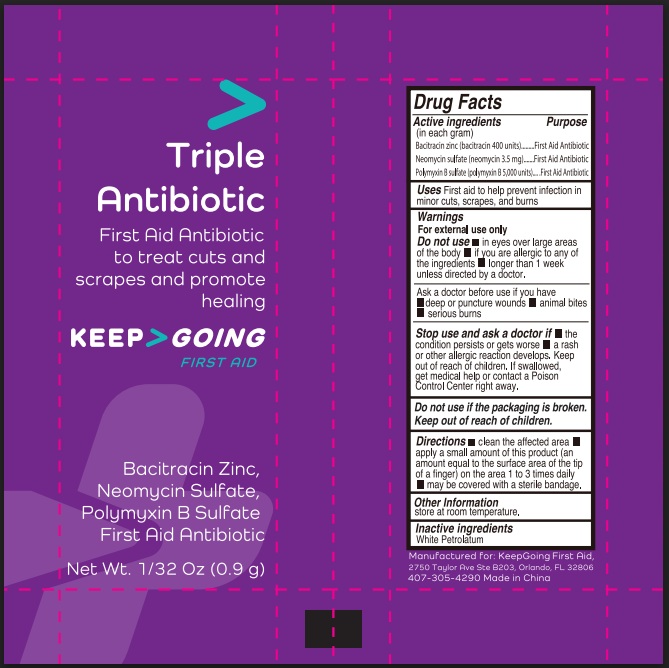 DRUG LABEL: Triple Antibiotic
NDC: 82942-1004 | Form: CREAM
Manufacturer: J&A Digital Inc.
Category: otc | Type: HUMAN OTC DRUG LABEL
Date: 20250807

ACTIVE INGREDIENTS: BACITRACIN ZINC 400 [CFU]/1 g; NEOMYCIN SULFATE 3.5 mg/1 g; POLYMYXIN B SULFATE 5000 [CFU]/1 g
INACTIVE INGREDIENTS: WHITE PETROLATUM

Triple Antibiotic

Active ingredients(in each gram)

Bacitracin zinc (bacitracin 400 units)

Neomycin sulfate (neomycin 3.5 mg)

Polymyxin B sulfate

(polymyxin B 5,000 units)

Purpose

first aid

antibiotic

Uses

first aid to help prevent infection in minor cuts, scrapes, and burns

Warnings

For external use only

Do not use

- in eyes over large areas of the body
- if you are allergic to any of the ingredients
- longer than 1 week unless directed by a doctor

Ask a doctor

before use if you have

- deep or puntucre wounds
- animal bites
- serious burns

Stop use and ask a doctor if

- the condition persists or gets worse
- a rash or other allergic reaction develops.

Keep out of reach of children.

if swallowed, get medical help or contact a Poison Control Center right away.

Directions

- clean the affected area
- apply a small amount of this product (an amount equal to the surface area of the tip of a finger) on the area 1 to 3 times daily
- may be covered with a sterile bandage.

Other Information

store at room temperature

Inactive ingredients

White petrolatum